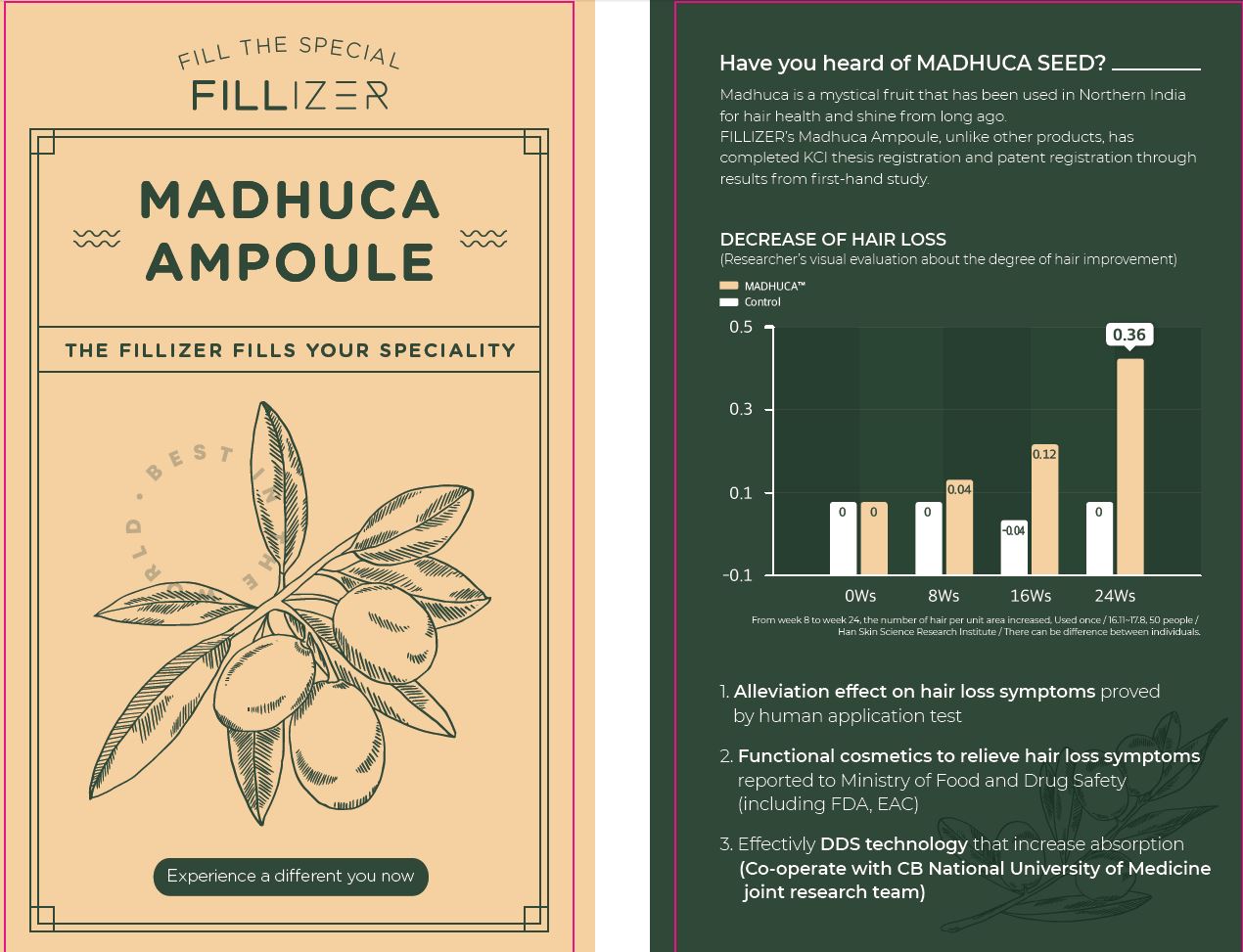 DRUG LABEL: FILLIZER MADHUCA AMPOULE
NDC: 81069-0001 | Form: LIQUID
Manufacturer: CJ ENM Co., Ltd.
Category: otc | Type: HUMAN OTC DRUG LABEL
Date: 20201113

ACTIVE INGREDIENTS: .ALPHA.-TOCOPHEROL ACETATE 2 g/100 mL; SALICYLIC ACID 0.495 g/100 mL; NIACINAMIDE 0.3 g/100 mL
INACTIVE INGREDIENTS: WATER

Drug Facts

ACTIVE INGREDIENT

salicylic acid, tocopheryl acetate, niacinamide

PURPOSE

antiseptic

KEEP OUT OF REACH OF THE CHILDREN

INDICATIONS AND USAGE

apply proper amount to the subject area

WARNINGS

■ For external use only.

■ Do not use in eyes.

■ lf swallowed, get medical help promptly.

■ Stop use, ask doctor lf irritation occurs.

■ Keep out of reach of children.

DOSAGE AND ADMINISTRATION

for external use only

INACTIVE INGREDIENT

Water
Alcohol
Polysorbate 80
Benzyl Glycol
Ammonium Acryloyldimethyltaurate/VP Copolymer
Avena Sativa (Oat) Leaf Extract
Trideceth-10
Salicylic Acid
Butylene Glycol
Madhuca Longifolia Sophorolipids(0.8%)
Fragrance
Hydrolyzed Collagen
Citrus Unshiu Peel Extract
Dipotassium Glycyrrhizate
Sodium Citrate
Ethylhexylglycerin
Pyridoxine HCl
1,2-Hexanediol
Raspberry Ketone
Menthol
Althaea Rosea Flower Extract
Coffea Arabica (Coffee) Seed Extract
Camellia Sinensis Leaf Extract
Morus Alba Bark Extract
Perilla Frutescens Leaf Extract
Houttuynia Cordata Extract
Polygonum Multiflorum Root Extract
Limonene
Geraniol
Citronellol
Butylphenyl Methylpropional
Linalool
Alpha-Isomethyl Ionone
Hydroxycitronellal
Amyl Cinnamal
Benzyl Benzoate
Citral